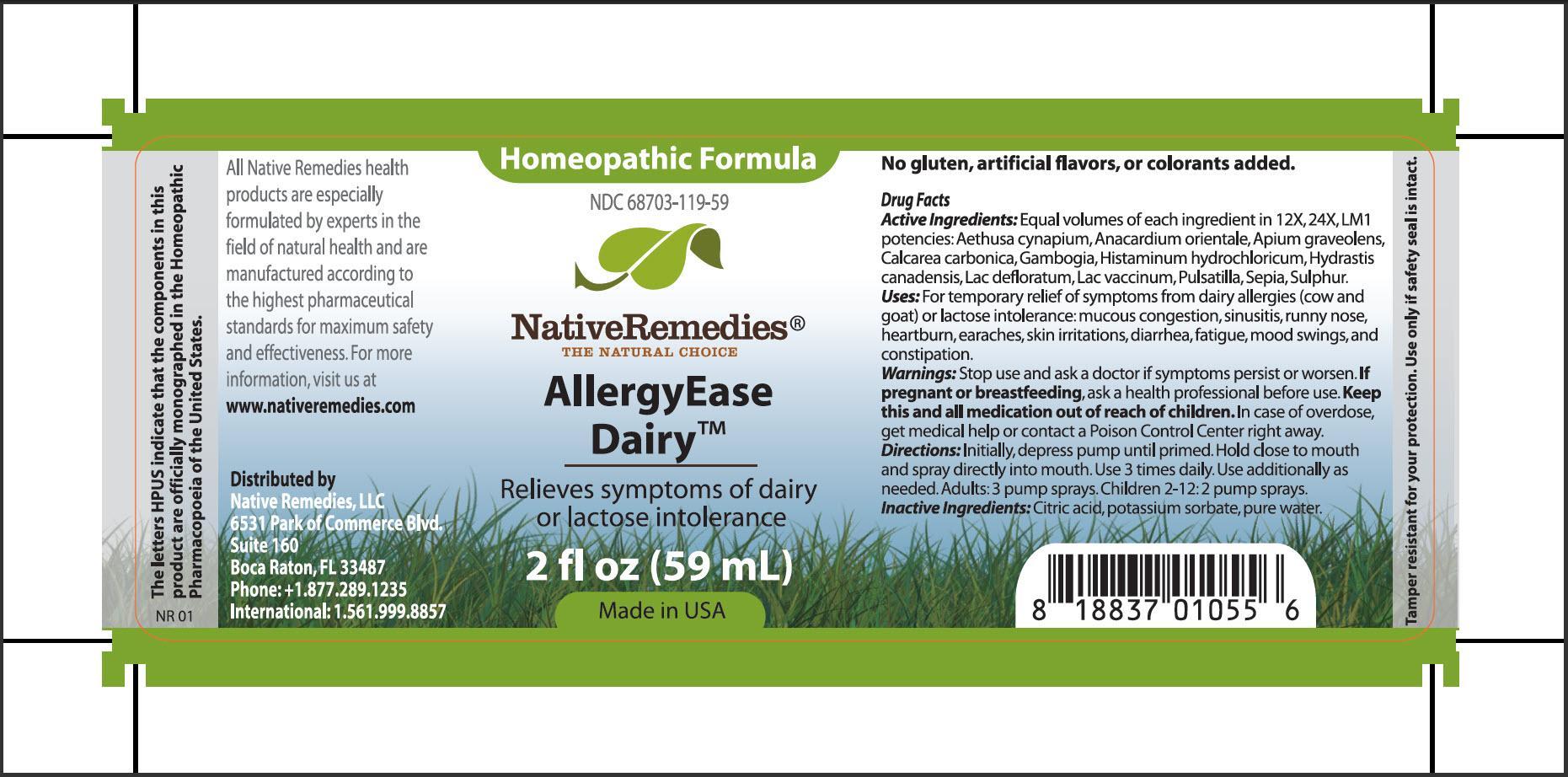 DRUG LABEL: AllergyEase Dairy
NDC: 68703-119 | Form: SPRAY
Manufacturer: Native Remedies, LLC
Category: homeopathic | Type: HUMAN OTC DRUG LABEL
Date: 20130612

ACTIVE INGREDIENTS: AETHUSA CYNAPIUM 12 [hp_X]/59 mL; SEMECARPUS ANACARDIUM JUICE 12 [hp_X]/59 mL; Celery seed 12 [hp_X]/59 mL; OYSTER SHELL CALCIUM CARBONATE, CRUDE 12 [hp_X]/59 mL; GAMBOGE  12 [hp_X]/59 mL; HISTAMINE DIHYDROCHLORIDE 12 [hp_X]/59 mL; GOLDENSEAL 12 [hp_X]/59 mL; SKIM MILK 12 [hp_X]/59 mL; COW MILK 12 [hp_X]/59 mL; PULSATILLA VULGARIS 12 [hp_X]/59 mL; SEPIA OFFICINALIS JUICE 12 [hp_X]/59 mL; SULFUR 12 [hp_X]/59 mL
INACTIVE INGREDIENTS: CITRIC ACID MONOHYDRATE; POTASSIUM SORBATE; WATER

AllergyEase Dairy

PURPOSE

Relieves symptoms of dairy or lactose intolerance

Drug Facts
Active Ingredients: Equal volumes of each ingredient in 12X, 24X, LM1 potencies: Aethusa cynapium, Anacardium orientale, Apium graveolens, Calcarea carbonica, Gambogia, Histaminum hydrochloricum, Hydrastis canadensis, Lac defloratum, Lac vaccinum, Pulsatilla, Sepia, Sulphur

INDICATIONS AND USAGE

Uses: For temporary relief of symptoms from dairy allergies (cow and goat) or lactose intolerance: mucous congestion, sinusitis, runny nose, heartburn, earaches, skin irritations, diarrhea, fatigue, mood swings, and constipation

WARNINGS

Warnings: Stop use and ask a doctor if symptoms persist or worsen

PREGNANCY OR BREAST FEEDING

If pregnant of breastfeeding, ask a health professional before use

KEEP OUT OF REACH OF CHILDREN

Keep this and all medication out of reach of children

OVERDOSAGE

In case of overdose, get medical help or contact a Poison Control Center right away

DOSAGE AND ADMINISTRATION

Directions: Initially, depress pump until primed. Hold close to mouth and spray directly into mouth. Use 3 times daily. Use additionally as needed. Adults: 3 pump sprays. Children 2-12:2 pump sprays

Inactive Ingredients: Citric acid, potassium sorbate, pure water

PATIENT COUNSELING INFORMATION

The letters HPUS indicate that the components in this product are officially monographed in the Homeopathic Pharmacopoeia of the United States

All Native Remedies health products are especially formulated by experts in the field of natural health and are manufactured according to the highest pharmaceutical standards for maximum safety and effectiveness. For more information, visit us at www.nativeremedies.com

Distributed by
Native Remedies, LLC
6531 Park of Commerce Blvd.
Suite 160
Boca Raton, FL 33487
International: 1.561.999.5587

No gluten, artificial flavors, or colorants added

STORAGE AND HANDLING

Tamper resistant for your protection. Use only if safety seal is intact